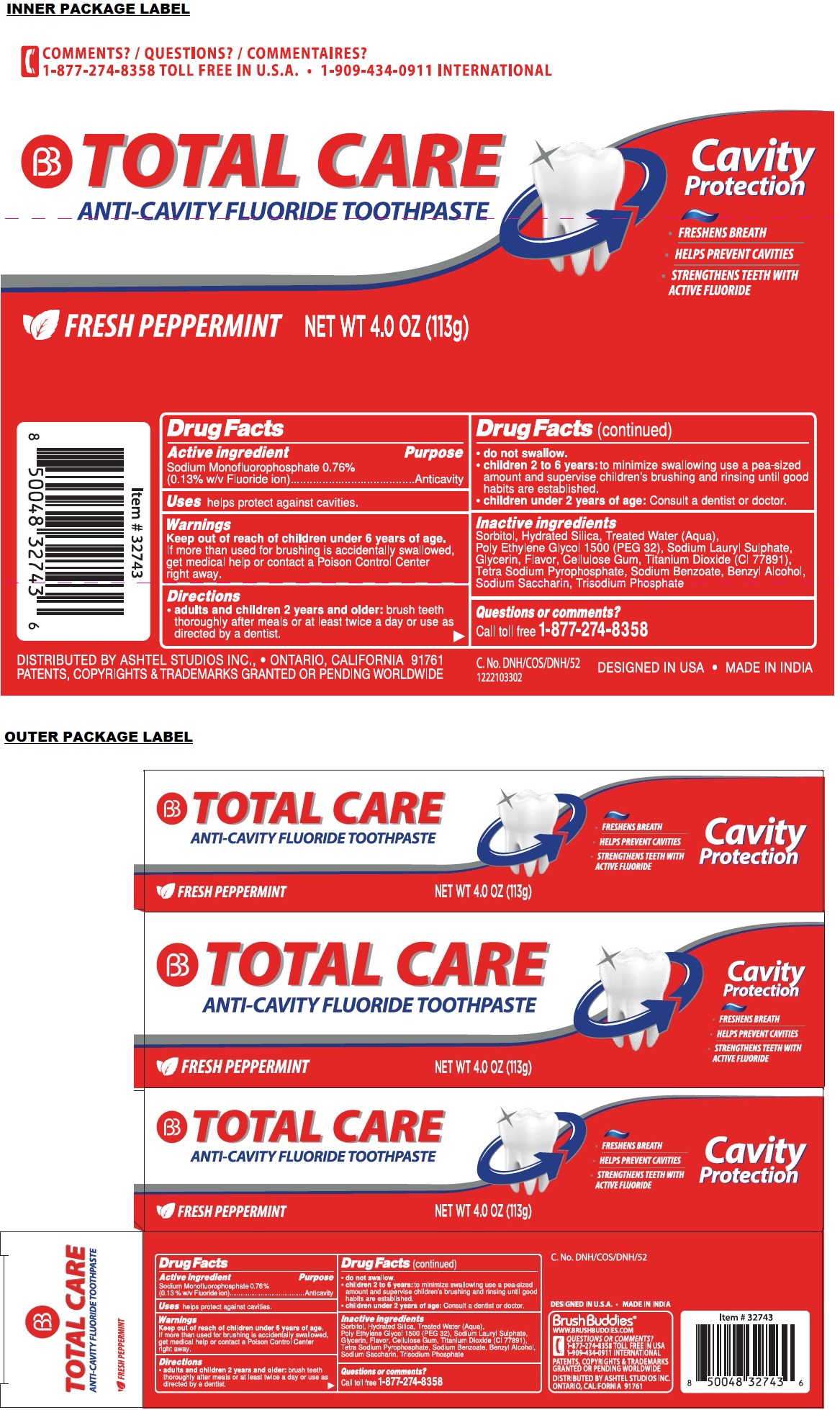 DRUG LABEL: Brush Buddies TOTAL CARE ANTI-CAVITY Protection
NDC: 70108-078 | Form: PASTE, DENTIFRICE
Manufacturer: Ashtel Studios, Inc.
Category: otc | Type: HUMAN OTC DRUG LABEL
Date: 20230922

ACTIVE INGREDIENTS: SODIUM MONOFLUOROPHOSPHATE 0.13 g/100 g
INACTIVE INGREDIENTS: SORBITOL; HYDRATED SILICA; WATER; POLYETHYLENE GLYCOL 1600; SODIUM LAURYL SULFATE; GLYCERIN; CARBOXYMETHYLCELLULOSE SODIUM, UNSPECIFIED; TITANIUM DIOXIDE; SODIUM PYROPHOSPHATE; SODIUM BENZOATE; BENZYL ALCOHOL; SACCHARIN SODIUM; SODIUM PHOSPHATE, TRIBASIC, ANHYDROUS

BB TOTAL CARE ANTI-CAVITY FLUORIDE TOOTHPASTE

Active ingredient

Sodium Monofluorophosphate 0.76%
(0.13% w/v Fluoride ion)

Purpose

Anticavity

Uses

helps protect against cavities.

Warnings

Keep out of reach of children under 6 years of age.
If more than used for brushing is accidentally swallowed, get medical help or contact a Poison Control Center right away.

Directions

• adults and children 2 years and older: brush teeth thoroughly after meals or at least twice a day or use as directed by a dentist.
• do not swallow.
• children 2 to 6 years: to minimize swallowing use a pea-sized amount and supervise children's brushing and rinsing until good habits are established.
• children under 2 years of age: Consult a dentist or doctor.

Inactive ingredients

Sorbitol, Hydrated Silica, Treated Water (Aqua), Poly Ethylene Glycol 1500 (PEG 32), Sodium Lauryl Sulphate, Glycerin, Flavor, Cellulose Gum, Titanium Dioxide (Cl 77891), Tetra Sodium Pyrophosphate, Sodium Benzoate, Benzyl Alcohol, Sodium Saccharin, Trisodium Phosphate

Questions or comments?

call toll free 1-877-274-8358

FRESH PEPPERMINT

ANTI-CAVITY FLUORIDE TOOTHPASTE

• FRESHENS BREATH
• STRENGTHENS TEETH WITH ACTIVE FLUORIDE

DESIGNED IN U.S.A. • MADE IN INDIA

Brush Buddies®
WWW.BRUSHBUDDIES.COM

QUESTIONS OR COMMENTS?
1-877-274-8358 TOLL FREE IN USA
1-909-434-0911 INTERNATIONAL

PATENTS, COPYRIGHTS & TRADEMARKS GRANTED OR PENDING WORLDWIDE

DISTRIBUTED BY ASHTEL STUDIOS INC.
ONTARIO, CALIFORNIA 91761